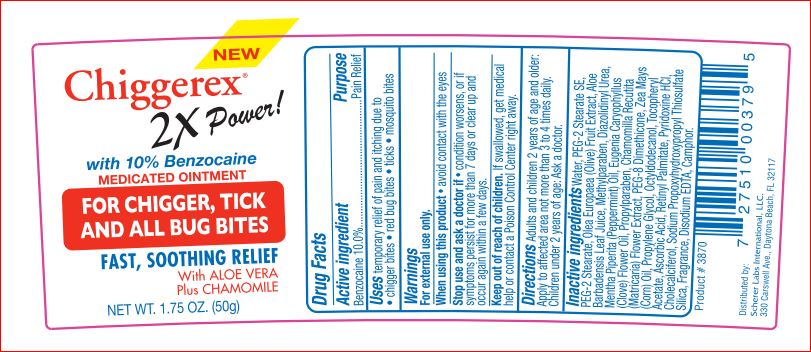 DRUG LABEL: Chiggerex 2X Medicated
NDC: 64048-1111 | Form: OINTMENT
Manufacturer: Product Quest Mfg
Category: otc | Type: HUMAN OTC DRUG LABEL
Date: 20171004

ACTIVE INGREDIENTS: Benzocaine 10 g/100 g
INACTIVE INGREDIENTS: Water; PEG-2 STEARATE; BLACK OLIVE; ALOE VERA LEAF; Methylparaben; Diazolidinyl Urea; PEPPERMINT OIL; CLOVE OIL; Propylparaben; CHAMOMILE; PEG-8 DIMETHICONE; CORN OIL; Propylene Glycol; Octyldodecanol; .ALPHA.-TOCOPHEROL ACETATE; Ascorbic Acid; VITAMIN A PALMITATE; PYRIDOXINE HYDROCHLORIDE; Cholecalciferol; SODIUM PROPOXYHYDROXYPROPYL THIOSULFATE SILICA; EDETATE DISODIUM; CAMPHOR (SYNTHETIC)

Drug Facts

Active ingredient Purpose

Benzocaine 10.0% Pain Relief

Uses

Temporarily relieves pain and itching due tochigger bites, red bug bites, ticks, mosquito bites

Warnings For external use only

When using this product avoid contact with the eyes

Stop use and ask a doctor if rash occurs
• condition worsens
• symptoms last more than 7 days or clear up and occur again within a few days

Keep out of reach of children. If swallowed, contact a Poison Control Center immediately.

Directions

• adults and children 12 years of age and older: apply to affected area, not more than 3 to 4 times daily. Children under 2 years of age: consult a doctor

Inactive ingredients

Water
PEG-2 Stearate SE, PEG-2 Stearate
Olea Europaea (Olive) Fruit Extract
Aloe Barbadensis Leaf Juice
Methylparaben
Diazolidinyl Urea
Mentha Piperita (Peppermint) Oil
Eugenia Caryophyllus (Clove) Flower Oil
Propylparaben
Chamomilla Recutita (Matricaria) Flower Extract
PEG-8 Dimethicone, Zea Mays (Corn) Oil, Propylene Glycol, Octyldodecanol, Tocopheryl
Acetate, Ascorbic Acid, Retinyl Palmitate, Pyridoxine HCl, Cholecalciferol, Sodium
Propoxyhydroxypropyl Thiosulfate Silica
Fragrance
Disodium EDTA
Camphor